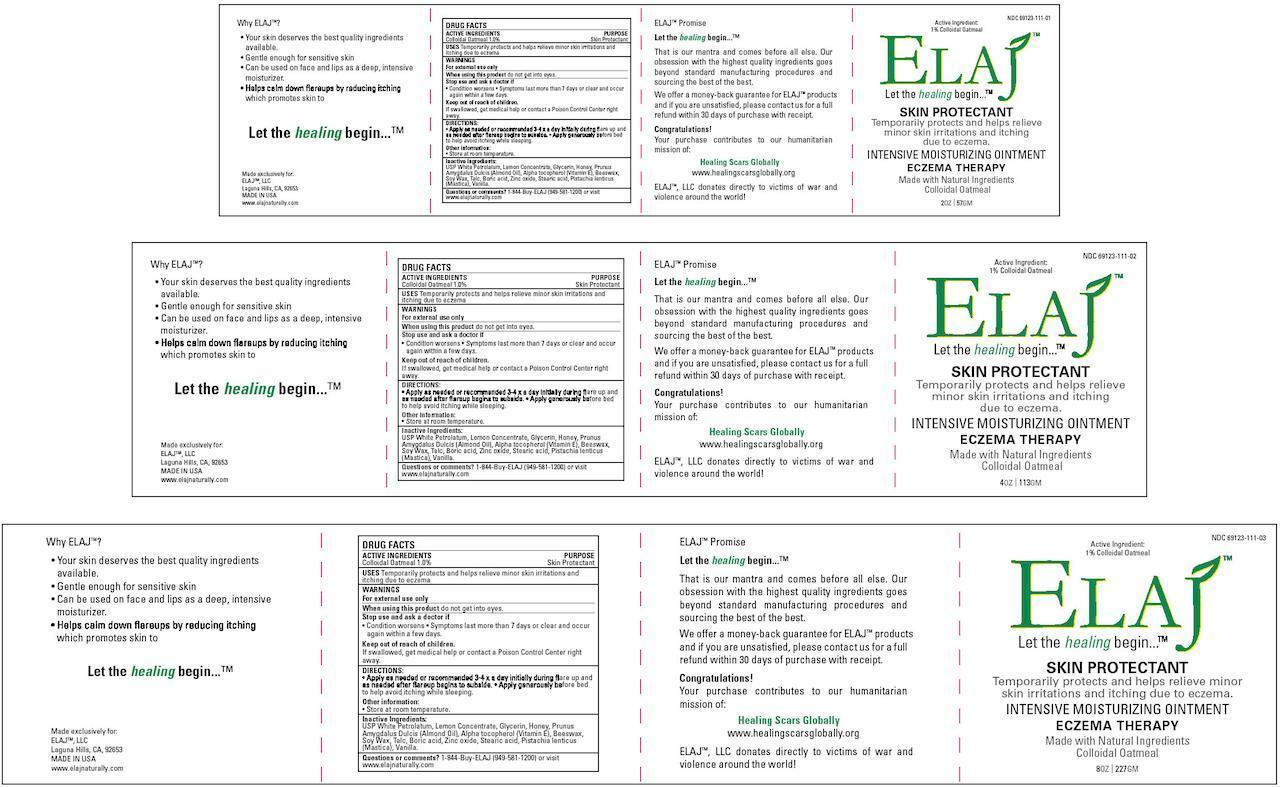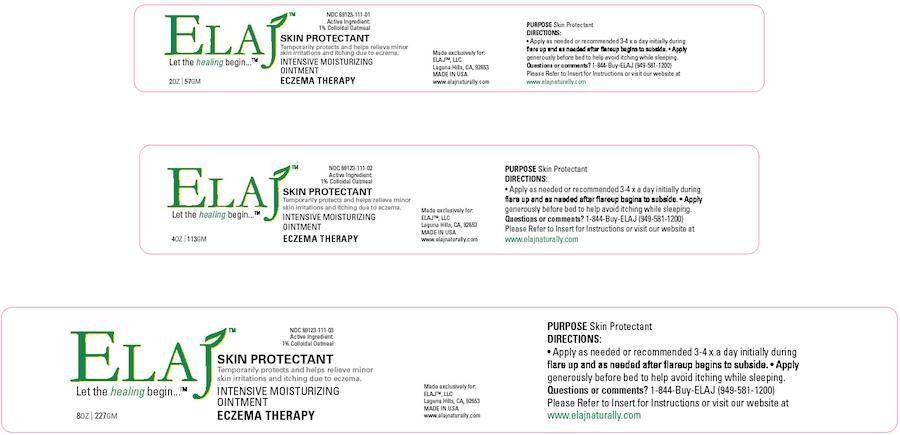 DRUG LABEL: Skin Protectant
NDC: 69123-111 | Form: OINTMENT
Manufacturer: ELAJ, LLC
Category: otc | Type: HUMAN OTC DRUG LABEL
Date: 20140725

ACTIVE INGREDIENTS: OATMEAL 0.57 g/57 g
INACTIVE INGREDIENTS: PETROLATUM; GLYCERIN; HONEY; ALMOND OIL; .ALPHA.-TOCOPHEROL; YELLOW WAX; Talc; BORIC ACID; ZINC OXIDE; STEARIC ACID; Vanilla

SKIN PROTECTANT

Active Ingredient

Colloidal Oatmeal 1.0%

Purpose

Skin Protectant

Uses

Temporarily protects and helps relieve minor skin irritations and itching due to eczema

WARNINGS

For external use only

When using this product

Do not get into eyes

Stop use and ask a doctor if

- Condition worsens
- Symptoms last more than 7 days or clear and occur again within a few days.

Keep out of reach of children

If swallowed, get medical help or contact a Poison Control Center right away

Directions

- Apply as needed or recommended 3-4 x a day initially during flare up and as needed after flareup begins to subside
- Apply generously before bed to help avoid itching while sleeping

Storage

Store at room temperature

Inactive Ingredients

USP White Petrolatum, Lemon Concentrate, Glycerin, Honey, Prunus Amygdalus Dulcis (Almond Oil), Alpha tocopherol (Vitamin E), Beeswax, Soy Wax, Talc, Boric acid, Zinc oxide, Stearic acid, Pistachia lenticus (Mastica), Vanilla

Questions or Comments

1-844-Buy-ELAJ (949-581-1200) or visit www.elajnaturally.com

Product Packaging Labels

57 g, 113 g, and 227 g Box Labels

57 g, 113 g, and 227 g Container Labels